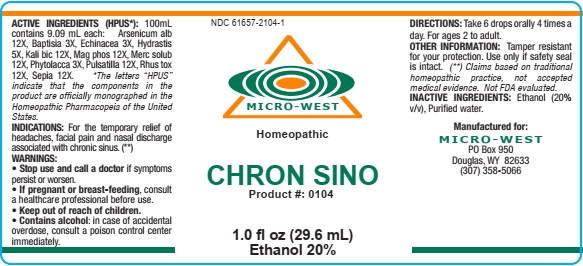 DRUG LABEL: CHRON SINO
NDC: 61657-0104 | Form: LIQUID
Manufacturer: WHITE MANUFACTURING INC. DBA MICRO WEST
Category: homeopathic | Type: HUMAN OTC DRUG LABEL
Date: 20190815

ACTIVE INGREDIENTS: ARSENIC TRIOXIDE 12 [hp_X]/30 mL; POTASSIUM DICHROMATE 12 [hp_X]/30 mL; MERCURIUS SOLUBILIS 12 [hp_X]/30 mL; PULSATILLA VULGARIS 12 [hp_X]/30 mL; SEPIA OFFICINALIS JUICE 12 [hp_X]/30 mL; ECHINACEA, UNSPECIFIED 3 [hp_X]/30 mL; GOLDENSEAL 3 [hp_X]/30 mL; PHYTOLACCA AMERICANA ROOT 3 [hp_X]/30 mL; BAPTISIA TINCTORIA 3 [hp_X]/30 mL; TOXICODENDRON PUBESCENS LEAF 12 [hp_X]/30 mL; MAGNESIUM PHOSPHATE, DIBASIC TRIHYDRATE 12 [hp_X]/30 mL
INACTIVE INGREDIENTS: ALCOHOL

DRUG FACTS

ACTIVE INGREDIENTS

Arsenicum alb 12X

Baptisia 3X

Echinacea 3X

Hydrastis 3X

Kali bic 12X

Mag phos 12X

Merc solub 12X

Phytolacca 3X

Pulsatilla 12X

Rhus tox 12X

Septia 12X

INACTIVE INGREDIENTS

Inactive ingredients: Alcohol (20% v/v), Purified water

PURPOSE

FOR THE TEMPORARY RELIEF OF HEADACHE, FACIAL PAIN, AND NASAL DISCHARGE ASSOCIATED WITH CHRONIC SINUS

KEEP OUT OF REACH OF CHILDREN

INDICATIONS

INDICATIONS: FOR THE TEMPORARY RELIEF OF HEADACHE, FACIAL PAIN, AND NASAL DISCHARGE ASSOCIATED WITH CHRONIC SINUS

WARNINGS

WARNING: Stop use and call a doctor if symptoms persist or worsen. If pregnant or breast-feeding, consult a healhcare professional before use. Contains alcohol: In case of accidental overdose, consult a poison control center immediately

OTHER SAFETY INFORMATION

OTHER INFORMATION: Tamper resistant for your protection. Use only if safety seal is intact

DIRECTIONS

DIRECTIONS: Take 6 drops orally, 4 times a day. For ages 2 to adult.

MANUFACTURE

MANUFACTURED FOR:

MICRO WEST

P.O. BOX 950

DOUGLAS, WY 82633

1-307-358-5066

label

NDC 61657-2104-1

MICRO-WEST

Homeopathic

CHRON SINO

Product #: 0104

1.0 fl oz (29.6 mL)

Ethanol 20%